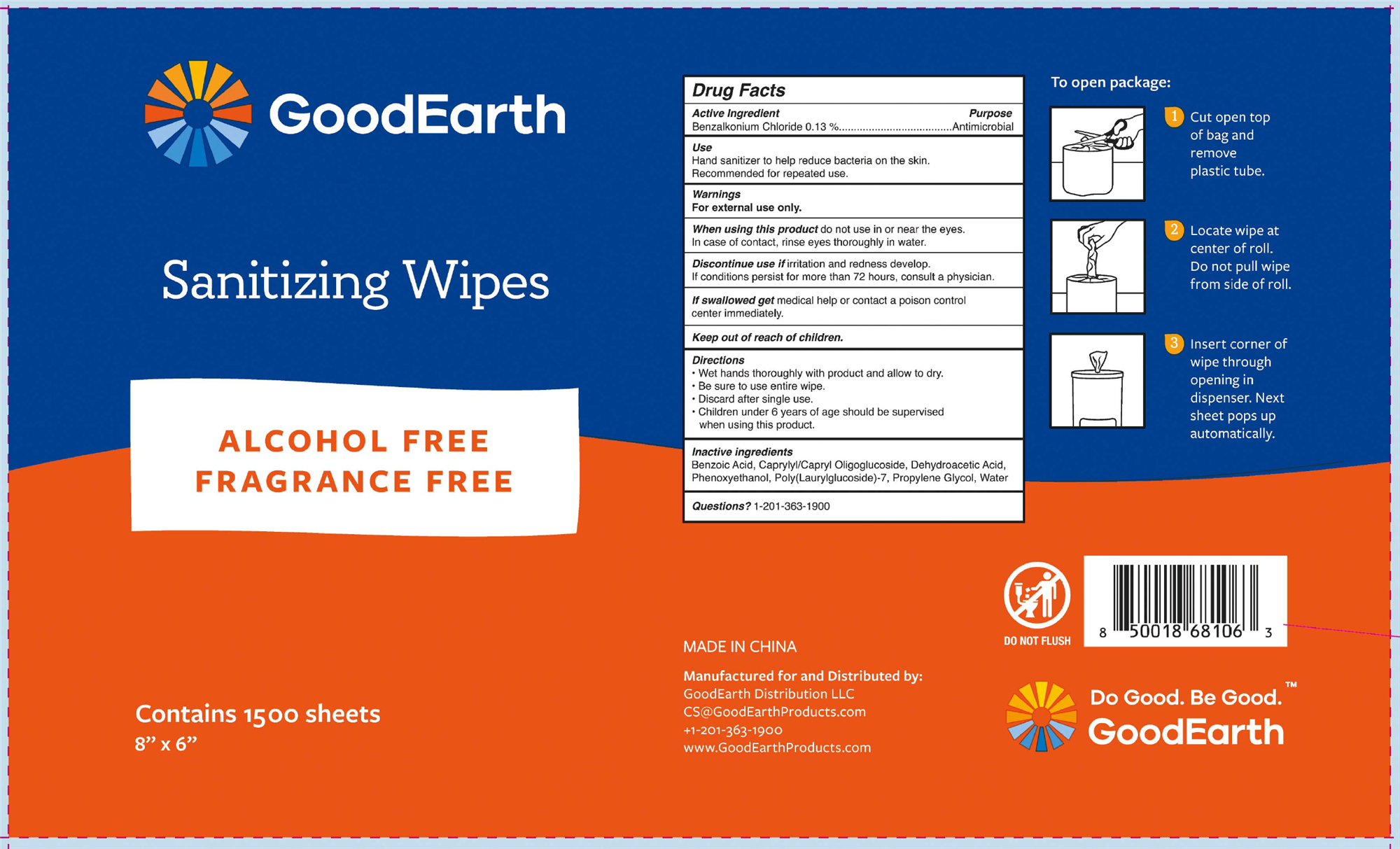 DRUG LABEL: GoodEarth Sanitizing Wipes
NDC: 71745-003 | Form: CLOTH
Manufacturer: GoodEarth Distribution LLC
Category: otc | Type: HUMAN OTC DRUG LABEL
Date: 20251224

ACTIVE INGREDIENTS: BENZALKONIUM CHLORIDE 3.822 mg/1 1
INACTIVE INGREDIENTS: PROPYLENE GLYCOL; DEHYDROACETIC ACID; POLY(LAURYLGLUCOSIDE)-7; BENZOIC ACID; WATER; PHENOXYETHANOL; CAPRYLYL/CAPRYL OLIGOGLUCOSIDE

71745-003 GoodEarth Sanitizing Wipes

Active Ingredient

Benzalkonium Chloride 0.13 %

Purpose

Antimicrobial

Use

Hand sanitizer to help reduce bacteria on the skin.

Recommended for repeated use.

Warnings

For external use only.

When using this product do not use in or near the eyes.

In case of contact, rinse eyes thoroughly in water.

Discontinue use if irritation and redness develop.

If conditions persist for more than 72 hours, consult a physician.

If swallowed get medical help or contact a poison control

center immediately.

Keep out of reach of children.

Directions

· Wet hands thoroughly with product and allow to dry.

· Be sure to use entire wipe.

· Discard after single use.

· Children under 6 years of age should be supervised

when using this product.

Inactive Ingredients

Benzoic Acid, Caprylyl/Capryl Oligoglucoside, Dehydroacetic Acid, Phenoxyethanol, Poly(Laurylglucoside)-7, Propylene Glycol, Water

PACKAGE LABEL

3000 Total Wipes (1500 wipes per roll; 2 rolls per case)

NDC: 71745-003-01